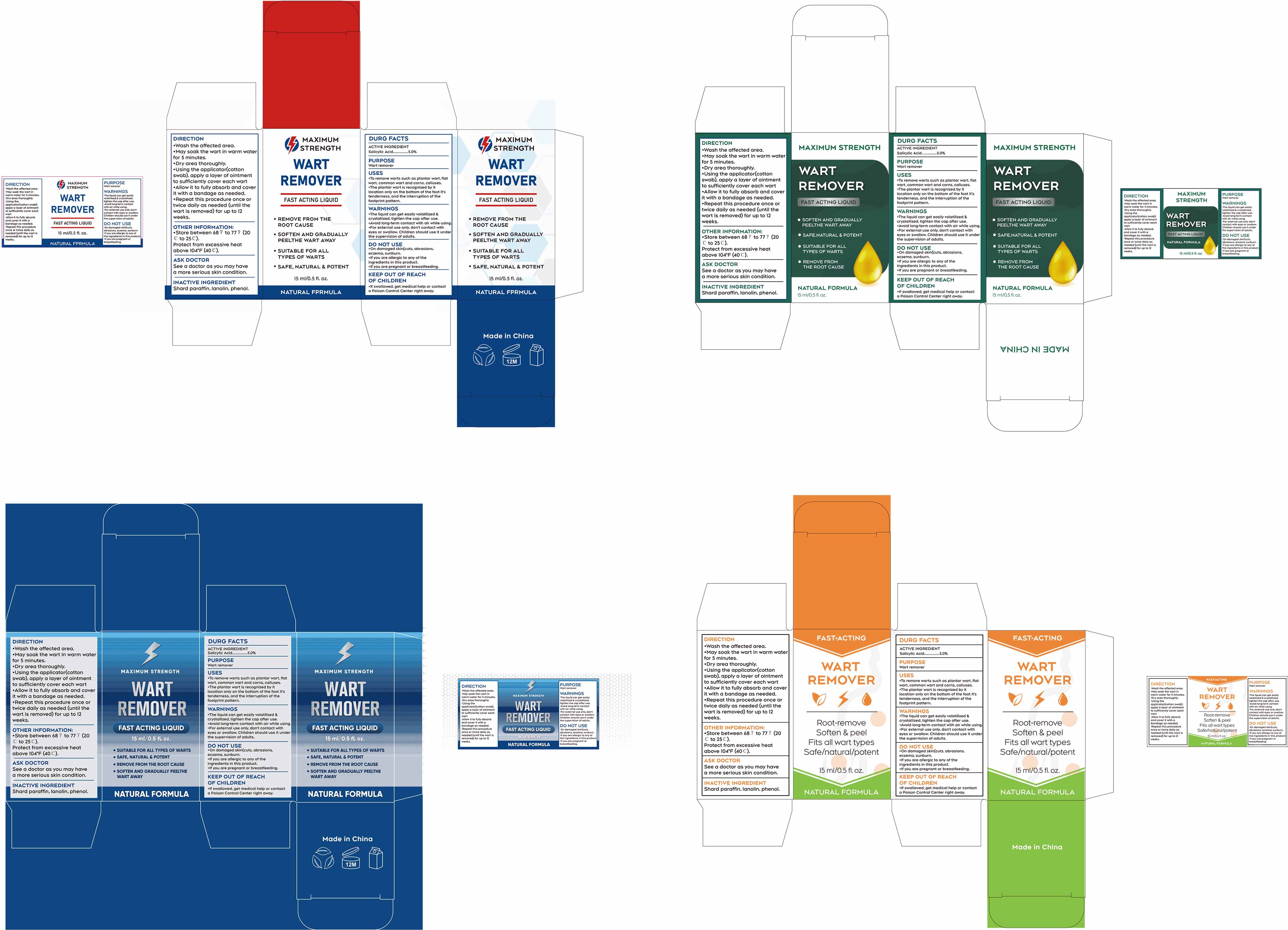 DRUG LABEL: WART REMOVER (salicylic acid) liquid
NDC: 85839-002 | Form: LIQUID
Manufacturer: Shenzhen Finona Information Technology Co., Ltd
Category: otc | Type: HUMAN OTC DRUG LABEL
Date: 20251204

ACTIVE INGREDIENTS: SALICYLIC ACID 0.05 g/1 mL
INACTIVE INGREDIENTS: PARAFFIN; LANOLIN; PHENOL

85839-002 WART REMOVER (salicylic acid) liquid

ACTIVE INGREDIENT

Salicylic Acid 5%

PURPOSE

Wart remover

INDICATIONS AND USAGE

.To remove warts such as plantar wart, flatwart. common wart and corns, calluses.
.The plantar wart is recognized by it location only on the bottom of the foot it's tenderness, and the interruption of the footprint pattern.

WARNINGS

The liquid can get easily volatilized & crystalllzed, tighten the cap after use.
Avoid long-term contact with alr while using.
For external use only,don't contact with eyes or swallow, Children should use it under the supervision of adults.

DO NOT USE

.On damaged skin(cuts.abrasions,eczema, sunburn.
.lf you are allergic to any of the ingredients in this product.
.lf you are pregnant or breastfeeding,

KEEP OUT OF REACH OF CHILDREN

.lf swallowed, get medical help or contact a Poison Control Center right away.

DOSAGE AND ADMINISTRATION

.Wash the affected area.
.May soak the wart in warm water for 5 minutes.
.Dry area thoroughly.
.Using the applicator(cotton swab),apply a layer of ointment to sufficiently cover each wart.
.Allow it to fully absorb and cover it with a bandage as needed.
.Repeat this procedure once or twice daily as needed (until the wart is removed) for up to 12 weeks.

INACTIVE INGREDIENT

Shard paraffin
lanolin
phenol